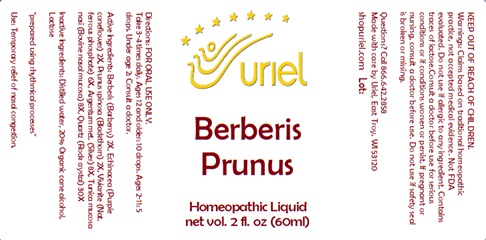 DRUG LABEL: Berberis Prunus
NDC: 48951-2140 | Form: LIQUID
Manufacturer: Uriel Pharmacy Inc.
Category: homeopathic | Type: HUMAN OTC DRUG LABEL
Date: 20240306

ACTIVE INGREDIENTS: ECHINACEA ANGUSTIFOLIA 2 [hp_X]/1 mL; SILVER 8 [hp_X]/1 mL; BERBERIS VULGARIS FRUIT 2 [hp_X]/1 mL; BOS TAURUS NASAL MUCOSA 8 [hp_X]/1 mL; SILICON DIOXIDE 30 [hp_X]/1 mL; SLOE 2 [hp_X]/1 mL; FERROSOFERRIC PHOSPHATE 6 [hp_X]/1 mL
INACTIVE INGREDIENTS: WATER; LACTOSE, UNSPECIFIED FORM; ALCOHOL

Berberis Prunus

INDICATIONS AND USAGE

Directions: FOR ORAL USE ONLY.

DOSAGE AND ADMINISTRATION

Take 3-4 times daily. Ages 12 and older: 10 drops. Ages 2-11: 5 drops. Under age 2: Consult a doctor.

ACTIVE INGREDIENT

Active Ingredients: Berberis (Barberry) 2X, Echinacea (Purple coneflower) 2X, Prunus spinosa (Blackthorn) 2X, Vivianite (Nat. ferrous phosphate) 6X, Argentum met. (Silver) 8X, Tunica mucosa nasi (Bovine nasal mucosa) 8X, Quartz (Rock crystal) 30X

INACTIVE INGREDIENT

Inactive Ingredients: Distilled water, 20% Organic cane alcohol, Lactose

"prepared using rhythmical processes"

PURPOSE

Use: Temporary relief of nasal congestion.

KEEP OUT OF REACH OF CHILDREN.

WARNINGS

Warnings: Claims based on traditional homeopathic practice, not accepted medical evidence. Not FDA evaluated. Do not use if allergic to any ingredient. Contains lactose. Consult a doctor before use for serious conditions or if conditions worsen or persist. If pregnant or nursing, consult a doctor before use. Do not use if safety seal is broken or missing.

Questions? Call 866.642.2858
Made with care by Uriel, East Troy, WI 53120
shopuriel.com Lot: